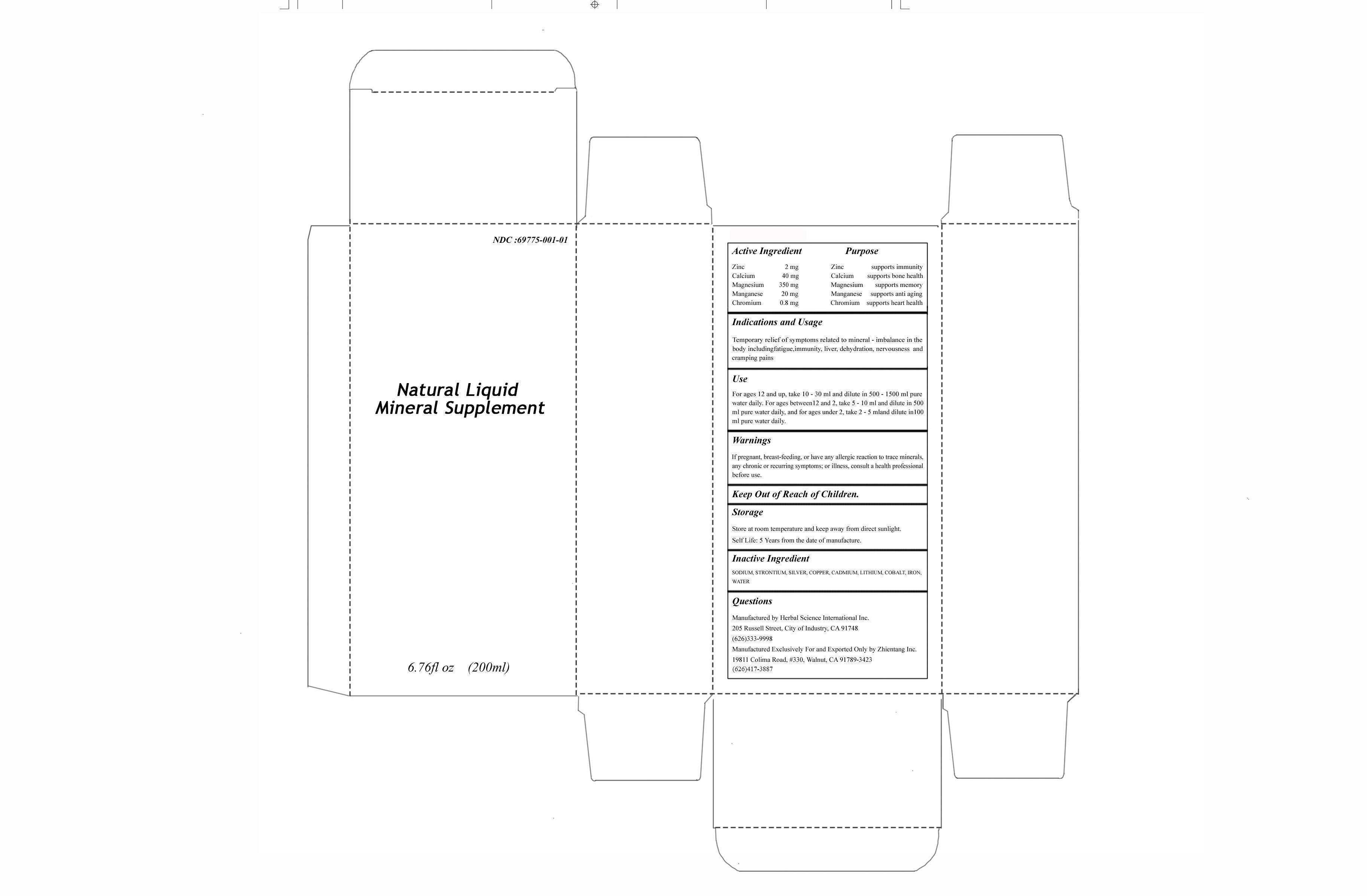 DRUG LABEL: Natural Liquid Mineral Supplement
NDC: 69775-001 | Form: LIQUID
Manufacturer: Herbal Science International Inc
Category: otc | Type: HUMAN OTC DRUG LABEL
Date: 20150820

ACTIVE INGREDIENTS: ZINC 2 mg/100 mL; CALCIUM 40 mg/100 mL; MAGNESIUM 350 mg/100 mL; MANGANESE 20 mg/100 mL; CHROMIUM 0.8 mg/100 mL
INACTIVE INGREDIENTS: SODIUM; STRONTIUM; SILVER; COPPER; CADMIUM; LITHIUM; COBALT; IRON; WATER

Herbal Science International Inc

Active Ingredient

Zinc 2 mg

Calcium 40 mg

Magnesium 350 mg

Manganese 20 mg

Chromium 0.8 mg

Purpose

Zinc supports immunity

Calcium supports bone health

Magnesium supports memory

Manganese supports anti aging

Chromium supports heart health

Indications and Usage

Temporary relief of symptoms related to mineral - imbalance in the body including fatigue, immunity, liver, dehydration, nervousness and cramping pains.

Use

For ages 12 and up, take 10 - 30 ml and dilute in 500 - 1500 ml pure water daily. For ages between 12 and 2, take 5 - 10 ml and dilute in 500 ml pure water daily, and for ages under 2, take 2 - 5 ml and dilute in 100 ml pure water daily.

Warnings

If pregnant, breast-feeding, or have any allergic reaction to trace minerals, any chronic or recurring symptoms; or illness, consult a health professional before use.

Keep Out of Reach of Children.

Storage

Store at room temperature and keep away from direct sunlight.

Self Life: 5 Years from the date of manufacture.

Questions or Comments?

Manufactured by Herbal Science International Inc.

205 Russell Street, City of Industry, CA 91748

Manufactured Exclusively For

and

Exported Only by Zhientang Inc

19811 Colima Road, #330, Walnut, CA 91789

(626)417-3887

Inactive Ingredient

SODIUM, STRONTIUM, SILVER, COPPER, CADMIUM, LITHIUM, COBALT, IRON, WATER